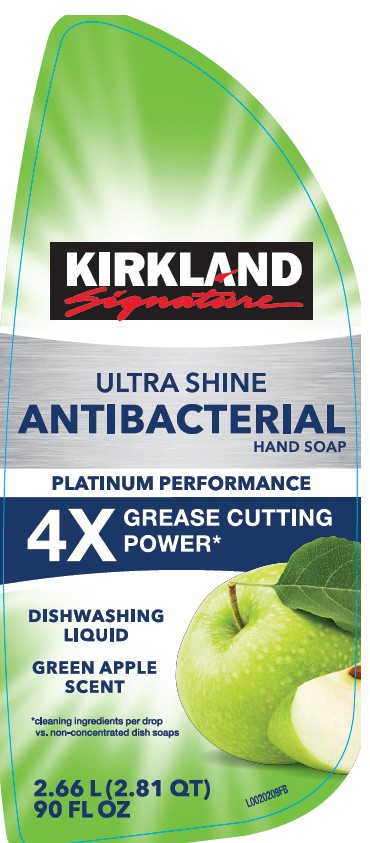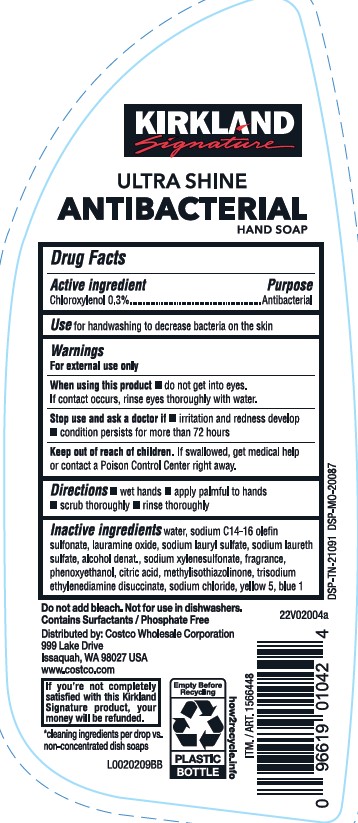 DRUG LABEL: dishwashing
NDC: 63981-933 | Form: LIQUID
Manufacturer: Costco Wholesale Corporation
Category: otc | Type: HUMAN OTC DRUG LABEL
Date: 20260202

ACTIVE INGREDIENTS: CHLOROXYLENOL 3 mg/1 mL
INACTIVE INGREDIENTS: FD&C BLUE NO. 1; WATER; SODIUM C14-16 OLEFIN SULFONATE; LAURAMINE OXIDE; SODIUM LAURYL SULFATE; SODIUM LAURETH SULFATE; ALCOHOL; SODIUM XYLENESULFONATE; PHENOXYETHANOL; CITRIC ACID MONOHYDRATE; METHYLISOTHIAZOLINONE; TRISODIUM ETHYLENEDIAMINE DISUCCINATE; SODIUM CHLORIDE; FD&C YELLOW NO. 5

Kirkland 993.000/993AA
Crisp Green Apple Antibacterial Hand Soap

Claims

KIRKLAND Signature

ULTRA SHINE

ANTIBACTERIAL

HAND SOAP

Active ingredient

Chloroxylenol 0.3%

Purpose

Antibacterial

Use

for handwashing to decrease bacteria on the skin

Warnings

For external use only

When using this product

- do not get into eyes. If contact occurs, rinse eyes thoroughly with water.

Stop use and ask a doctor if

- irritation and redness develop

- condition persists for more than 72 hours

Keep out of reach of children.

If swallowed, get medical help or contact a Poison Control Center right away.

Directions

- wet hands
- apply palmful to hands
- scrub thoroughly
- rinse thoroughly

Inactive ingredients

water, sodium C14-16 olefin sulfonate, lauramine oxide, sodium lauryl sulfate, sodium laureth sulfate, alcohol denat., sodium xylenesulfonate, fragrance, phenoxyethanol, citric acid, methylisothiazolinone, trisodium ethylenediamine disuccinate, sodium chloride, yellow 5, blue 1

Do not add bleach. Not for use in dishwashers.

Contains Surfactants / Phosphate Free

Distributed by: Costco Wholesale Corporation

999 Lake Drive

Issaquah,WA 98027 USA

www.costco.com

If you're not completely satisified with this Kirkland Signature product, your money will be refunded.

*cleaning ingredients per drop vs. non-concentrated dish soaps.

Empty Before Recycling

PLASTIC BOTTLE

how2recycle.info

DSP-TN-21091 DSP-MO-20087

Principal display panel

KIRKLAND SIGNATURE

ULTRA SHINE

ANTIBACTERIAL HAND SOAP

PLATINUM PERFORMANCE

4x GREASE CUTTING POWER*

DISHWASHING LIQUID

GREEN APPLE SCENT

*cleaning ingredients per drop vs. non-concentrated dish soaps

2.66 L (2.81 QT) 90 FL OZ